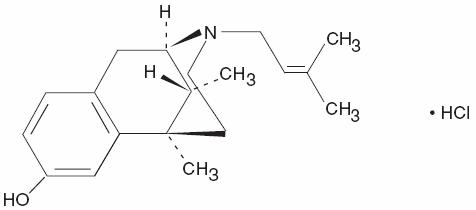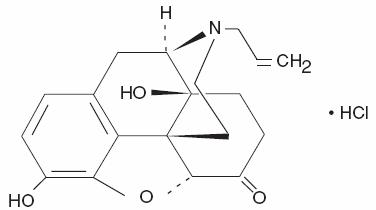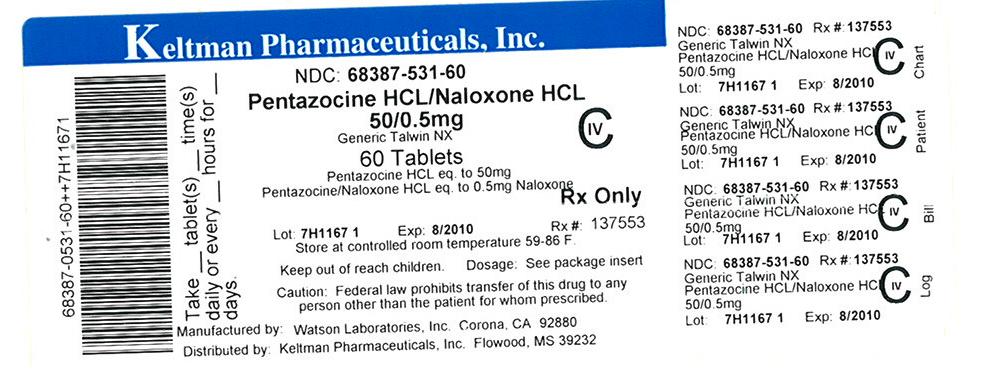 DRUG LABEL: Pentazocine and naloxone
NDC: 68387-531 | Form: TABLET
Manufacturer: Keltman Pharmaceuticals Inc.
Category: prescription | Type: HUMAN PRESCRIPTION DRUG LABEL
Date: 20100720

ACTIVE INGREDIENTS: PENTAZOCINE HYDROCHLORIDE 50 mg/1 1; NALOXONE HYDROCHLORIDE 0.5 mg/1 1
INACTIVE INGREDIENTS: SILICON DIOXIDE; ANHYDROUS DIBASIC CALCIUM PHOSPHATE; D&C YELLOW NO. 10; FD&C BLUE NO. 1; FD&C YELLOW NO. 6; MAGNESIUM STEARATE; CELLULOSE, MICROCRYSTALLINE; STARCH, CORN; SODIUM LAURYL SULFATE

Pentazocine and
Naloxone
Hydrochlorides
Tablets USP
Rx only

SPL UNCLASSIFIED SECTION

Analgesic for Oral use Only

Pentazocine and naloxone hydrochlorides tablets are intended for oral use only. Severe, potentially lethal, reactions may result from misuse of pentazocine and naloxone hydrochlorides tablets by injection either alone or in combination with other substances. (See DRUG ABUSE AND DEPENDENCE section.)

DESCRIPTION

Pentazocine and naloxone hydrochlorides tablets USP contain pentazocine hydrochloride USP, equivalent to 50 mg base, a member of the benzazocine series (also known as the benzomorphan series), and naloxone hydrochloride USP, equivalent to 0.5 mg base.

Pentazocine and naloxone hydrochlorides tablets are an analgesic for oral administration.

Chemically, pentazocine hydrochloride is (2R*, 6R*, 11R*)-1,2,3,4,5,6-Hexahydro-6,11-dimethyl-3-(3-methyl-2-butenyl)-2,6-methano-3-benzazocin-8-ol hydrochloride, a white, crystalline substance soluble in acidic aqueous solutions. It has the following structural formula:

C19H27NO•HCI Molecular Weight 321.88

Chemically, naloxone hydrochloride is 17-AIlyl-4,5α-epoxy-3,14-dihydroxymorphinan-6-one hydrochloride. It is a slightly off-white powder, and is soluble in water and dilute acids. It has the following structural formula:

C19H21N04•HCI Molecular Weight 363.84

Each tablet, for oral administration, contains pentazocine hydrochloride USP, equivalent to 50 mg of pentazocine, and naloxone hydrochloride USP, equivalent to 0.5 mg of naloxone. In addition each tablet contains the following inactive ingredients: colloidal silicon dioxide, dibasic calcium phosphate, D&C Yellow No. 10 Al-lake, FD&C Blue No. 1 Al-lake, FD&C Yellow No. 6 Al-lake, magnesium stearate, microcrystalline cellulose, pregelatinized starch, and sodium lauryl sulfate.

CLINICAL PHARMACOLOGY

Pentazocine is a potent analgesic which when administered orally in a 50 mg dose appears equivalent in analgesic effect to 60 mg (1 grain) of codeine. Onset of significant analgesia usually occurs between 15 and 30 minutes after oral administration, and duration of action is usually three hours or longer. Onset and duration of action and the degree of pain relief are related both to dose and the severity of pretreatment pain. Pentazocine weakly antagonizes the analgesic effects of morphine and meperidine; in addition, it produces incomplete reversal of cardiovascular, respiratory, and behavioral depression induced by morphine and meperidine. Pentazocine has about 1/50 the antagonistic activity of nalorphine. It also has sedative activity.

Pentazocine is well absorbed from the gastrointestinal tract. Concentrations in plasma coincide closely with the onset, duration, and intensity of analgesia; peak values occur 1 to 3 hours after oral administration. The half-life in plasma is 2 to 3 hours.

Pentazocine is metabolized in the liver and excreted primarily in the urine. Pentazocine passes into the fetal circulation.

Naloxone when administered orally at 0.5 mg has no pharmacologic activity. Naloxone hydrochloride administered parenterally at the same dose is an effective antagonist to pentazocine and a pure antagonist to narcotic analgesics.

Pentazocine and naloxone hydrochlorides tablets are a potent analgesic when administered orally. However the presence of naloxone in pentazocine and naloxone naloxone hydrochlorides tablets will prevent the effect of pentazocine if the product is misused by injection.

Studies in animals indicate that the presence of naloxone does not affect pentazocine analgesia when the combination is given orally. If the combination is given by injection the action of pentazocine is neutralized.

INDICATIONS AND USAGE

Pentazocine and naloxone hydrochlorides tablets are intended for oral use only. Severe, potentially lethal, reactions may result from misuse of pentazocine and naloxone hydrochlorides tablets by injection either alone or in combination with other substances. (See DRUG ABUSE AND DEPENDENCE section.)

Pentazocine and naloxone hydrochlorides tablets are indicated for the relief of moderate to severe pain.

Pentazocine and naloxone hydrochlorides tablets are indicated for oral use only.

CONTRAINDICATIONS

Pentazocine and naloxone hydrochlorides tablets should not be administered to patients who are hypersensitive to either pentazocine or naloxone.

Pentazocine and naloxone hydrochlorides tablets are intended for oral use only. Severe, potentially lethal, reactions may result from misuse of pentazocine and naloxone hydrochlorides tablets by injection either alone or in combination with other substances. (See DRUG ABUSE AND DEPENDENCE section.)

WARNINGS

Drug Dependence. Pentazocine can cause a physical and psychological dependence. (See DRUG ABUSE AND DEPENDENCE.)

Head Injury and Increased Intracranial Pressure. As in the case of other potent analgesics, the potential of pentazocine for elevating cerebrospinal fluid pressure may be attributed to CO2 retention due to the respiratory depressant effects of the drug. These effects may be markedly exaggerated in the presence of head injury, other intracranial lesions, or a pre-existing increase in intracranial pressure. Furthermore, pentazocine can produce effects which may obscure the clinical course of patients with head injuries. In such patients, pentazocine must be used with extreme caution and only if its use is deemed essential.

Usage with Alcohol. Due to the potential for increased CNS depressant effects, alcohol should be used with caution in patients who are currently receiving pentazocine.

Patients Receiving Narcotics. Pentazocine is a mild narcotic antagonist. Some patients previously given narcotics, including methadone for the daily treatment of narcotic dependence, have experienced withdrawal symptoms after receiving pentazocine.

Certain Respiratory Conditions. Although respiratory depression has rarely been reported after oral administration of pentazocine, the drug should be administered with caution to patients with respiratory depression from any cause, severely limited respiratory reserve, severe bronchial asthma, and other obstructive respiratory conditions, or cyanosis.

Acute CNS Manifestations. Patients receiving therapeutic doses of pentazocine have experienced hallucinations (usually visual), disorientation, and confusion which have cleared spontaneously within a period of hours. The mechanism of this reaction is not known. Such patients should be very closely observed and vital signs checked. If the drug is reinstituted, it should be done with caution since these acute CNS manifestations may recur.

PRECAUTIONS

CNS Effect

Caution should be used when pentazocine is administered to patients prone to seizures; seizures have occurred in a few such patients in association with the use of pentazocine though no cause and effect relationship has been established.

Impaired Renal or Hepatic Function

Decreased metabolism of pentazocine by the liver in extensive liver disease may predispose to accentuation of side effects. Although laboratory tests have not indicated that pentazocine causes or increases renal or hepatic impairment, the drug should be administered with caution to patients with such impairment.

In prescribing pentazocine for long-term use, the physician should take precautions to avoid increases in doses by the patient.

Biliary Surgery

Narcotic drug products are generally considered to elevate biliary tract pressure for varying periods following their administration. Some evidence suggests that pentazocine may differ from other marketed narcotics in this respect (i.e., it causes little or no elevation in biliary tract pressures). The clinical significance of these findings, however, is not yet known.

Information for Patients

Since sedation, dizziness, and occasional euphoria have been noted, ambulatory patients should be warned not to operate machinery, drive cars, or unnecessarily expose themselves to hazards. Pentazocine may cause physical and psychological dependence when taken alone and may have additive CNS depressant properties when taken in combination with alcohol or other CNS depressants.

Myocardial Infarction

As with all drugs, pentazocine should be used with caution in patients with myocardial infarction who have nausea or vomiting.

Drug Interactions

Usage with Alcohol: See WARNINGS.

Carcinogenesis, Mutagenesis, Impairment of Fertility

No long-term studies in animals to test for carcinogenesis have been performed with the components of pentazocine and naloxone hydrochlorides tablets.

Pregnancy Category C

Animal reproduction studies have not been conducted with pentazocine and naloxone hydrochlorides. It is also not known whether pentazocine and naloxone hydrochlorides tablets can cause fetal harm when administered to pregnant women or can affect reproduction capacity. Pentazocine and naloxone hydrochlorides tablets should be given to pregnant women only if clearly needed. However, animal reproduction studies with pentazocine have not demonstrated teratogenic or embryotoxic effects.

Labor and Delivery

Patients receiving pentazocine during labor have experienced no adverse effects other than those that occur with commonly used analgesics. Pentazocine and naloxone hydrochlorides tablets should be used with caution in women delivering premature infants. The effect of pentazocine and naloxone hydrochlorides tablets on the mother and fetus, the duration of labor and delivery, the possibility that forceps delivery or other intervention or resuscitation of the newborn may be necessary, or the effect of pentazocine and naloxone hydrochlorides tablets on the later growth, development, and functional maturation of the child are unknown at the present time.

Nursing Mothers

It is not known whether this drug is excreted in human milk. Because many drugs are excreted in human milk, caution should be exercised when pentazocine and naloxone hydrochlorides tablets are administered to a nursing woman.

Pediatric Use

Safety and effectiveness in pediatric patients below the age of 12 years have not been established.

Geriatric Use

Controlled clinical studies of pentazocine and naloxone hydrochlorides tablets did not include sufficient numbers of subjects aged 65 and over to determine whether they respond differently from younger subjects. Other reported clinical experience has not identified differences in responses or effectiveness in analgesic activity between the elderly and younger patients. In general, dose selection for an elderly patient should be cautious, usually starting at the low end of the dosing range, reflecting the greater frequency of decreased hepatic, renal, or cardiac function, and of concomitant disease or other drug therapy.

ADVERSE REACTIONS

Cardiovascular: Hypotension, tachycardia, syncope.

Respiratory: Rarely, respiratory depression.

Acute CNS Manifestations: Patients receiving therapeutic doses of pentazocine have experienced hallucinations (usually visual), disorientation, and confusion which have cleared spontaneously within a period of hours. The mechanism of this reaction is not known. Such patients should be closely observed and vital signs checked. If the drug is reinstituted it should be done with caution since these acute CNS manifestations may recur.

Other CNS Effects: Dizziness, lightheadedness, hallucinations, sedation, euphoria, headache, confusion, disorientation; infrequently weakness, disturbed dreams, insomnia, syncope, visual blurring and focusing difficulty, depression; and rarely tremor, irritability, excitement, tinnitus.

Autonomic: Sweating; infrequently flushing; and rarely chills.

Gastrointestinal: Nausea, vomiting, constipation, diarrhea, anorexia, rarely abdominal distress.

Allergic: Edema of the face; dermatitis, including pruritus; flushed skin, including plethora; infrequently rash, and rarely urticaria.

Ophthalmic: Visual blurring and focusing difficulty.

Hematologic: Depression of white blood cells (especially granulocytes), which is usually reversible, moderate transient eosinophilia.

Other: Headache, chills, insomnia, weakness, urinary retention, paresthesia, serious skin reactions, including erythema multiforme, Stevens-Johnson Syndrome and toxic epidermal necrolysis.

DRUG ABUSE AND DEPENDENCE

Controlled Substance. Pentazocine and naloxone hydrochlorides tablets are a Schedule IV controlled substance.

There have been some reports of dependence and of withdrawal symptoms with orally administered pentazocine. Patients with a history of drug dependence should be under close supervision while receiving pentazocine orally. There have been rare reports of possible abstinence syndromes in newborns after prolonged use of pentazocine during pregnancy.

There have been instances of psychological and physical dependence on parenteral pentazocine in patients with a history of drug abuse and rarely, in patients without such a history. Abrupt discontinuance following the extended use of parenteral pentazocine has resulted in withdrawal symptoms.

In prescribing pentazocine for chronic use, the physician should take precautions to avoid increases in dose by the patient.

The amount of naloxone present in pentazocine and naloxone hydrochlorides tablets (0.5 mg per tablet) has no action when taken orally and will not interfere with the pharmacologic action of pentazocine. However, this amount of naloxone given by injection has profound antagonistic action to narcotic analgesics.

Severe, even lethal, consequences may result from misuse of tablets by injection either alone or in combination with other substances, such as pulmonary emboli, vascular occlusion, ulceration and abscesses, and withdrawal symptoms in narcotic dependent individuals.

Pentazocine and naloxone hydrochlorides tablets contain an opioid antagonist, naloxone (0.5 mg). Naloxone is inactive when administered orally at this dose, and its inclusion in pentazocine and naloxone hydrochlorides tablets is intended to curb a form of misuse of oral pentazocine. Parenterally, naloxone is an active narcotic antagonist. Thus, pentazocine and naloxone hydrochlorides tablets have a lower potential for parenteral misuse than the previous oral pentazocine hydrochloride formulation. However, it is still subject to patient misuse and abuse by the oral route.

OVERDOSAGE

Manifestations. Clinical experience of overdosage with this oral medication has been insufficient to define the signs of this condition.

Treatment. Oxygen, intravenous fluids, vasopressors, and other supportive measures should be employed as indicated. Assisted or controlled ventilation should also be considered. For respiratory depression due to overdosage or unusual sensitivity to pentazocine, parenteral naloxone is a specific and effective antagonist.

Pentazocine and naloxone hydrochlorides tablets are intended for oral use only. Severe, potentially lethal, reactions may result from misuse of pentazocine and naloxone hydrochlorides tablets by injection either alone or in combination with other substances. (See DRUG ABUSE AND DEPENDENCE section.)

DOSAGE AND ADMINISTRATION

Adults. The usual initial adult dose is 1 tablet every three or four hours. This may be increased to 2 tablets when needed. Total daily dosage should not exceed 12 tablets.

When anti-inflammatory or antipyretic effects are desired in addition to analgesia, aspirin can be administered concomitantly with this product.

Pediatric Patients. Since clinical experience in pediatric patients under 12 years of age is limited, administration of this product in this age group is not recommended.

Duration of Therapy. Patients with chronic pain who receive pentazocine and naloxone hydrochlorides tablets orally for prolonged periods have only rarely been reported to experience withdrawal symptoms when administration was abruptly discontinued (see WARNINGS). Tolerance to the analgesic effect of pentazocine has also been reported only rarely. However, there is no long-term experience with the oral administration of pentazocine and naloxone hydrochlorides tablets.

HOW SUPPLIED

Pentazocine and Naloxone Hydrochlorides Tablets USP are light green, scored, capsule shaped tablets debossed 395 to the left of the score, 50 over 0.5 to the right of the score and WATSON on the reverse side.

They are supplied by Keltman Pharmaceuticals Inc. as follows:

NDC | Strength | Quantity/Form | Color | Source Prod. Code
68387-531-30 | 50 mg / 0.5 mg | 30 Tablets in a Plastic Bottle | light green | 0591-0395
68387-531-60 | 50 mg / 0.5 mg | 60 Tablets in a Plastic Bottle | light green | 0591-0395
68387-531-12 | 50 mg / 0.5 mg | 120 Tablets in a Plastic Bottle | light green | 0591-0395

Store at controlled room temperature 15°-30°C (59°-86°F). [See USP.]

Dispense in a tight, light-resistant container as defined in the USP.

Watson Laboratories, Inc.
Corona, CA 92880 USA

This Product was Repackaged By Sandhills Packaging For:

Keltman Pharmaceuticals Inc.
1 Lakeland Square, Suite A
Flowood, MS 39232
United States